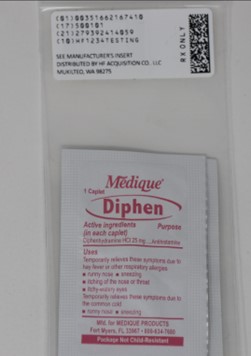 DRUG LABEL: diphenhydramine hydrochloride
NDC: 51662-1674 | Form: TABLET, FILM COATED
Manufacturer: HF Acquisition Co LLC, DBA HealthFirst
Category: otc | Type: HUMAN OTC DRUG LABEL
Date: 20251121

ACTIVE INGREDIENTS: DIPHENHYDRAMINE HYDROCHLORIDE 25 mg/1 1
INACTIVE INGREDIENTS: MICROCRYSTALLINE CELLULOSE; POLYETHYLENE GLYCOL, UNSPECIFIED; D&C RED NO. 27; LACTOSE, UNSPECIFIED FORM; CROSCARMELLOSE SODIUM; HYPROMELLOSE, UNSPECIFIED; MAGNESIUM STEARATE; SILICON DIOXIDE; TITANIUM DIOXIDE

ACTIVE INGREDIENT

Diphenhydramine Hydrochloride 25 mg

PURPOSE

Antihistamine

USES

Temporarily relieves these symptoms due to hay fever or other respiratory allergies

runny nose
sneezing
itching of the nose or throat
itchy, watery eyes

Temporarily relieves these symptoms due to the common cold

runny nose
sneezing

Do not use – Diphen Allergy Caplet

to make a child sleepy
with any other product containing diphenhydramine, even one that is used on skin.

Ask a doctor before use if you have – Diphen Allergy Caplet

a breathing problem such as emphysema or chronic bronchitis
trouble urinating due to an enlarged prostate gland
glaucoma

Ask a doctor or pharmacist before use if you are – Diphen Allergy Caplet

taking sedatives or tranquilizers

When using this product – Diphen Allergy Caplet

marked drowsiness may occur
avoid alcoholic drinks
alcohol, sedatives and tranquilizers may increase the drowsiness effect
use caution when driving a motor vehicle or operating machinery
excitability may occur, especially in children

If pregnant or breast-feeding, – Diphen Allergy Caplet

ask a health care professional before use.

Keep out of reach of children. – Diphen Allergy Caplet

In case of overdose, contact a physician or poison control center right away (1-800-222-1222).

DIRECTIONS

Do not use – Diphen Allergy Caplet
to make a child sleepy
with any other product containing diphenhydramine, even one that is used on skin.
Ask a doctor before use if you have – Diphen Allergy Caplet
a breathing problem such as emphysema or chronic bronchitis
trouble urinating due to an enlarged prostate gland
glaucoma
Ask a doctor or pharmacist before use if you are – Diphen Allergy Caplet
taking sedatives or tranquilizers
When using this product – Diphen Allergy Caplet
marked drowsiness may occur
avoid alcoholic drinks
alcohol, sedatives and tranquilizers may increase the drowsiness effect
use caution when driving a motor vehicle or operating machinery
excitability may occur, especially in children
If pregnant or breast-feeding, – Diphen Allergy Caplet
ask a health care professional before use.

Keep out of reach of children. – Diphen Allergy Caplet
In case of overdose, contact a physician or poison control center right away (1-800-222-1222).

OTHER SAFETY INFORMATION

protect from light
store at room temperature 68º-77ºF (20º-25ºC)
tamper-evident sealed packets
do not use any opened or torn packets

INACTIVE INGREDIENT

croscarmellose sodium, D&C red #27 aluminum lake, hypromellose, lactose, magnesium stearate, microcrystalline cellulose, polyethylene glycol, silicon dioxide, titanium dioxide

KEEP OUT OF THE REACH OF CHILDREN

Do not use – Diphen Allergy Caplet

to make a child sleepy
with any other product containing diphenhydramine, even one that is used on skin.

Ask a doctor before use if you have – Diphen Allergy Caplet

a breathing problem such as emphysema or chronic bronchitis
trouble urinating due to an enlarged prostate gland
glaucoma

Ask a doctor or pharmacist before use if you are – Diphen Allergy Caplet

taking sedatives or tranquilizers

When using this product – Diphen Allergy Caplet

marked drowsiness may occur
avoid alcoholic drinks
alcohol, sedatives and tranquilizers may increase the drowsiness effect
use caution when driving a motor vehicle or operating machinery
excitability may occur, especially in children

If pregnant or breast-feeding, – Diphen Allergy Caplet

ask a health care professional before use.

DOSAGE AND ADMINISTRATION

Temporarily relieves these symptoms due to hay fever or other respiratory allergies

runny nose
sneezing
itching of the nose or throat
itchy, watery eyes

Temporarily relieves these symptoms due to the common cold

runny nose
sneezing

INDICATIONS AND USAGE

Temporarily relieves these symptoms due to hay fever or other respiratory allergies

runny nose
sneezing
itching of the nose or throat
itchy, watery eyes

Temporarily relieves these symptoms due to the common cold

runny nose
sneezing